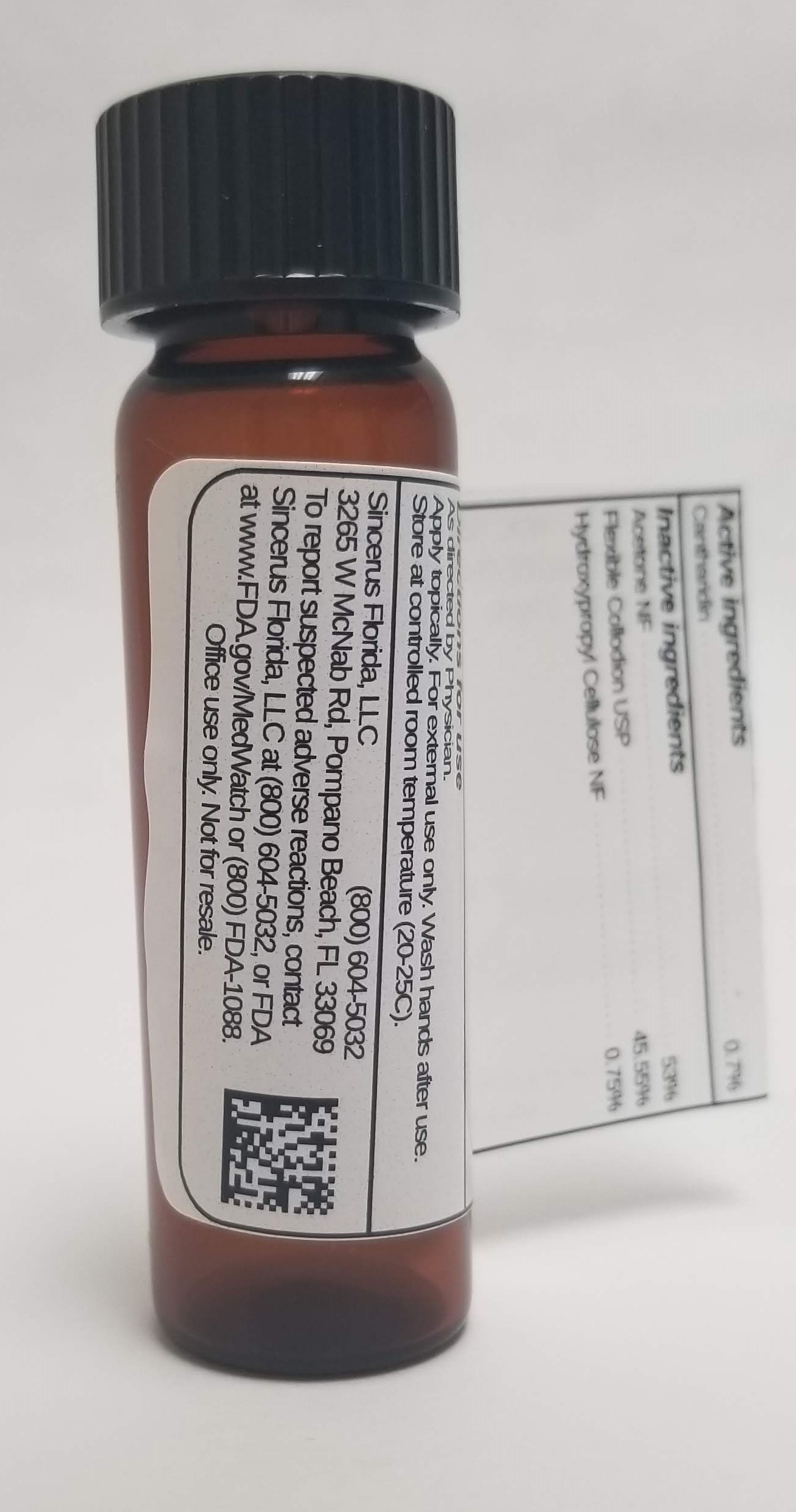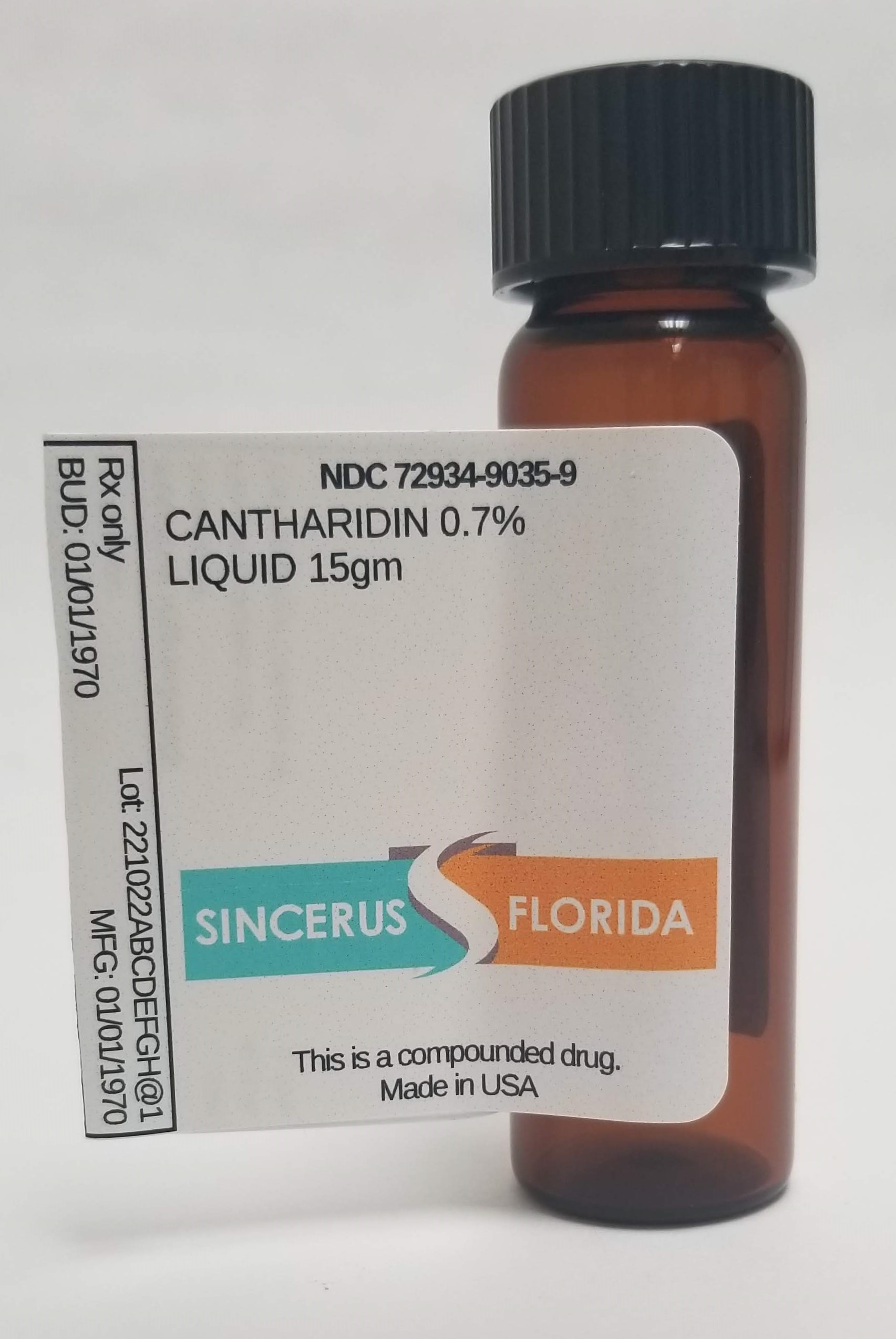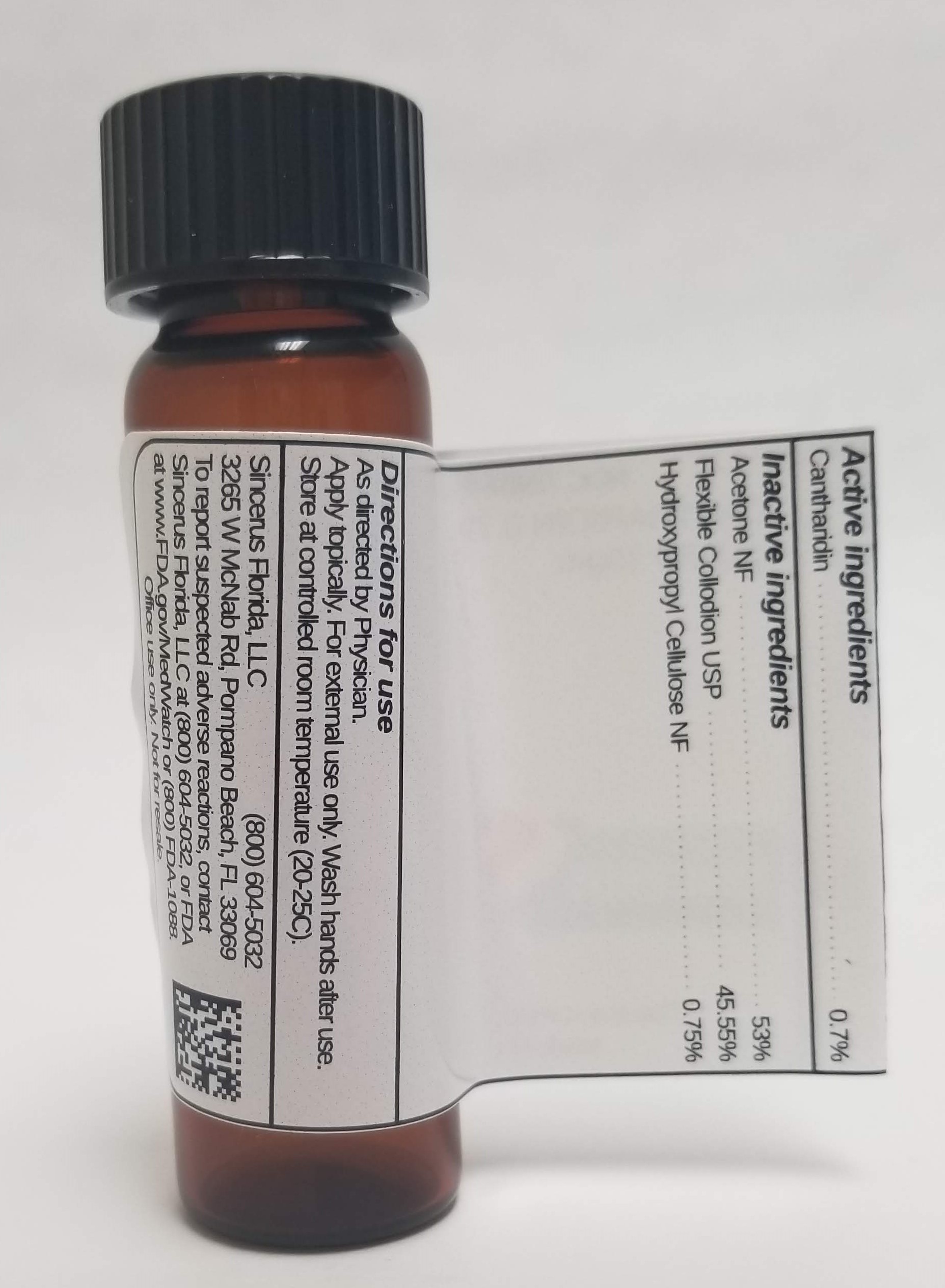 DRUG LABEL: CANTHARIDIN 0.7%
NDC: 72934-9035 | Form: LIQUID
Manufacturer: Sincerus Florida, LLC
Category: prescription | Type: HUMAN PRESCRIPTION DRUG LABEL
Date: 20190517

ACTIVE INGREDIENTS: CANTHARIDIN 0.7 g/100 g

CANTHARIDIN 0.7%